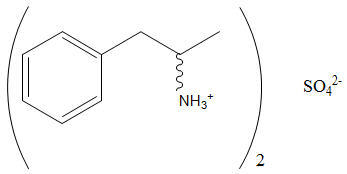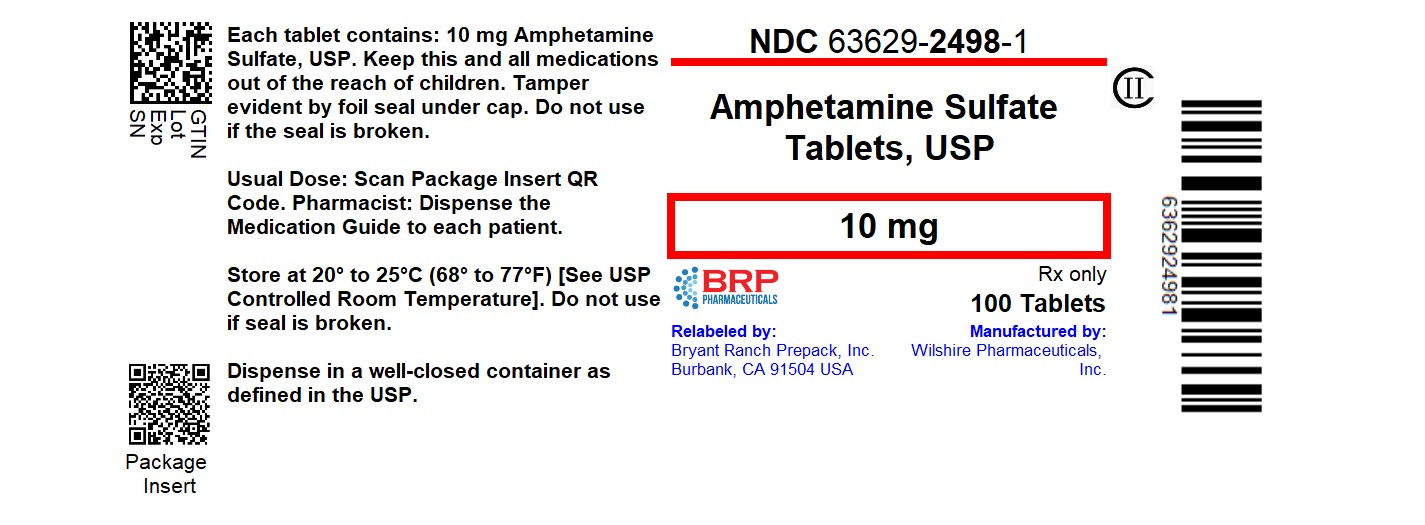 DRUG LABEL: Amphetamine Sulfate
NDC: 63629-2498 | Form: TABLET
Manufacturer: Bryant Ranch Prepack
Category: prescription | Type: HUMAN PRESCRIPTION DRUG LABEL
Date: 20250818
DEA Schedule: CII

ACTIVE INGREDIENTS: AMPHETAMINE SULFATE 10 mg/1 1
INACTIVE INGREDIENTS: CROSPOVIDONE; MICROCRYSTALLINE CELLULOSE; STEARIC ACID; FD&C BLUE NO. 1

AMPHETAMINE SULFATE TABLETS, USP, CII

WARNING

AMPHETAMINES HAVE A HIGH POTENTIAL FOR ABUSE. ADMINISTRATION OF AMPHETAMINES FOR PROLONGED PERIODS OF TIME MAY LEAD TO DRUG DEPENDENCE AND MUST BE AVOIDED. PARTICULAR ATTENTION SHOULD BE PAID TO THE POSSIBILITY OF SUBJECTS OBTAINING AMPHETAMINES FOR NON-THERAPEUTIC USE OR DISTRIBUTION TO OTHERS, AND THE DRUGS SHOULD BE PRESCRIBED OR DISPENSED SPARINGLY.

MISUSE OF AMPHETAMINE MAY CAUSE SUDDEN DEATH AND SERIOUS CARDIOVASCULAR ADVERSE EVENTS.

DESCRIPTION

Amphetamine Sulfate is a sympathomimetic amino of the amphetamine group. It is a white, odorless crystalline powder. It has a slightly bitter taste. Its solutions are acid to litmus, having a pH of 5.0 to 6.0. It is freely soluble in water and slightly soluble in alcohol.

Each tablet, for oral administration contains 5 mg or 10 mg of amphetamine sulfate. Each tablet also contains the following inactive ingredients: crospovidone, silicified microcrystalline cellulose and stearic acid. The 10 mg tablet also contains FD&C Blue #1.

Structural Formula:

C18H28N2SO4

MW 368.49

CLINICAL PHARMACOLOGY

Amphetamines are non-catecholamine, sympathomimetic amines with CNS stimulant activity. Peripheral actions include elevations of systolic and diastolic blood pressures, and weak bronchodilator, and respiratory stimulant action.

Amphetamine, as the racemic form, differs from dextroamphetamine in a number of ways. The l-isomer is more potent than the d-isomer in cardiovascular activity, but much less potent in causing CNS excitatory effects. The racemic mixture also is less effective as an appetite suppressant when compared to dextroamphetamine. There is neither specific evidence which clearly establishes the mechanism whereby amphetamines produce mental and behavioral effects in children, nor conclusive evidence regarding how those effects relate to the condition of the central nervous system.

Drugs in this class used in obesity are commonly known as "anorectics" or "anorexigenics." It has not been established, however, that the action of such drugs in treating obesity is primarily one of appetite suppression. Other central nervous system actions or metabolic effects, may be involved, for example. Adult obese subjects instructed in dietary management and treated with "anorectic" drugs lose more weight on the average than these treated with placebo and diet, as determined in relatively short- term clinical trials.

The magnitude of increased weight loss of drug-treated patients over placebo-treated patients is only a fraction of a pound a week. The rate of weight loss is greatest in the first weeks of therapy for both drug and placebo subjects and tends to decrease in succeeding weeks. The origins of the increased weight loss due to the various possible drug effects are not established. The amount of weight loss associated with the use of an "anorectic" drug varies from trial to trial, and the increased weight loss appears to be related in part to variables other than the drug prescribed, such as the physician-investigator, the population treated, and the diet prescribed. Studies do not permit conclusions as to the relative importance of the drug and nondrug factors on weight loss.

The natural history of obesity is measured in years, whereas the studies cited are restricted to few weeks duration; thus, the total impact of drug-induced weight loss over that of diet alone must be considered clinically limited.

INDICATIONS AND USAGE

Amphetamine Sulfate Tablets, USP, are indicated for:

1. Narcolepsy
2. Attention Deficit Disorder with Hyperactivity as an integral part of a total treatment program which typically includes other remedial measures (psychological, educational, social) for a stabilizing effect in children with behavioral syndrome characterized by the following group of developmentally inappropriate symptoms: moderate to severe distractibility, short attention span, hyperactivity, emotional lability, and impulsivity. The diagnosis of the syndrome should not be made with finality when these symptoms are only of comparatively recent origin. Nonlocalizing (soft) neurological signs, learning disability, and abnormal EEG may or may not be present, and a diagnosis of central nervous system dysfunction may or not be warranted.
3. Exogenous Obesity as a short term (a few weeks) adjunct in a regimen of weight reduction based on caloric restriction for patients refractory to alternative therapy, e.g., repeated diets, group programs, and other drugs. The limited usefulness of amphetamines (see CLINICAL PHARMACOLOGY) should be weighed against possible risks inherent in use of the drug, such as those described below.

CONTRAINDICATIONS

Advanced arteriosclerosis, symptomatic cardiovascular disease, moderate to severe hypertension, hyperthyroidism, known hypersensitivity or idiosyncrasy to the sympathomimetic amines.

Agitated states.

Patients with a history of drug abuse.

During or within 14 days following the administration of monoamine oxidase inhibitors (hypertensive crises may result).

WARNING

Serious Cardiovascular Events

Sudden Death and Pre-Existing Structural Cardiac Abnormalities or Other Serious Heart Problems

Children and Adolescents

Sudden death has been reported in association with CNS stimulant treatment at usual doses in children and adolescents with structural cardiac abnormalities or other serious heart problems. Although some serious heart problems alone carry an increased risk of sudden death, stimulant products generally should not be used in children or adolescents with known serious structural cardiac abnormalities, cardiomyopathy, serious heart rhythm abnormalities, or other serious cardiac problems that may place them at increased vulnerability to the sympathomimetic effects of a stimulant drug (see CONTRAINDICATIONS).

Adults

Sudden deaths, stroke, and myocardial infarction have been reported in adults taking stimulant drugs at usual doses for ADHD. Although the role of stimulants in these adult cases is also unknown, adults have a greater likelihood than children of having serious structural cardiac abnormalities, cardiomyopathy, serious heart rhythm abnormalities, coronary artery disease, or other serious cardiac problems. Adults with such abnormalities should also generally not be treated with stimulant drugs (see CONTRAINDICATIONS).

Hypertension and other Cardiovascular Conditions

Stimulant medications cause a modest increase in average blood pressure (about 2 to 4 mmHg) and average heart rate (about 3 to 6 bpm), and individuals may have larger increases. While the mean changes alone would not be expected to have short-term consequences, all patients should be monitored for larger changes in heart rate and blood pressure. Caution is indicated in treating patients whose underlying medical conditions might be compromised by increases in blood pressure or heart rate, e.g., those with pre-existing hypertension, heart failure, recent myocardial infarction, or ventricular arrhythmia (see CONTRAINDICATIONS).

Assessing Cardiovascular Status in Patients being Treated with Stimulant Medications

Children, adolescents, or adults who are being considered for treatment with stimulant medications should have a careful history (including assessment for a family history of sudden death or ventricular arrhythmia) and physical exam to assess for the presence of cardiac disease, and should receive further cardiac evaluation if findings suggest such disease (e.g., electrocardiogram and echocardiogram). Patients who develop symptoms such as exertional chest pain, unexplained syncope, or other symptoms suggestive of cardiac disease during stimulant treatment should undergo a prompt cardiac evaluation.

Psychiatric Adverse Events

Pre-Existing Psychosis

Administration of stimulants may exacerbate symptoms of behavior disturbance and thought disorder in patients with a pre-existing psychotic disorder.

Bipolar Illness

Particular care should be taken in using stimulants to treat ADHD in patients with comorbid bipolar disorder because of concern for possible induction of a mixed/manic episode in such patients. Prior to initiating treatment with a stimulant, patients with comorbid depressive symptoms should be adequately screened to determine if they are at risk for bipolar disorder; such screening should include a detailed psychiatric history, including a family history of suicide, bipolar disorder, and depression.

Emergence of New Psychotic or Manic Symptoms

Treatment emergent psychotic or manic symptoms, e.g., hallucinations, delusional thinking, or mania in children and adolescents without a prior history of psychotic illness or mania can be caused by stimulants at usual doses. If such symptoms occur, consideration should be given to a possible causal role of the stimulant, and discontinuation of treatment may be appropriate. In a pooled analysis of multiple short-term, placebo-controlled studies, such symptoms occurred in about 0.1% (4 patients with events out of 3482 exposed to methylphenidate or amphetamine for several weeks at usual doses) of stimulant-treated patients compared to 0 in placebo-treated patients.

Aggression

Aggressive behavior or hostility is often observed in children and adolescents with ADHD, and has been reported in clinical trials and the postmarketing experience of some medications indicated for the treatment of ADHD. Although there is no systematic evidence that stimulants cause aggressive behavior or hostility, patients beginning treatment for ADHD should be monitored for the appearance of or worsening of aggressive behavior or hostility.

Long-Term Suppression of Growth

Careful follow-up of weight and height in children ages 7 to 10 years who were randomized to either methylphenidate or non-medication treatment groups over 14 months, as well as in naturalistic subgroups of newly methylphenidate-treated and non-medication treated children over 36 months (to the ages of 10 to 13 years), suggests that consistently medicated children (i.e., treatment for 7 days per week throughout the year) have a temporary slowing in growth rate (on average, a total of about 2 cm less growth in height and 2.7 kg less growth in weight over 3 years), without evidence of growth rebound during this period of development. Published data are inadequate to determine whether chronic use of amphetamines may cause a similar suppression of growth, however, it is anticipated that they likely have this effect as well. Therefore, growth should be monitored during treatment with stimulants, and patients who are not growing or gaining height or weight as expected may need to have their treatment interrupted.

Seizures

There is some clinical evidence that stimulants may lower the convulsive threshold in patients with prior history of seizures, in patients with prior EEG abnormalities in absence of seizures, and, very rarely, in patients without a history of seizures and no prior EEG evidence of seizures. In the presence of seizures, the drug should be discontinued.

Peripheral Vasculopathy, including Raynaud's phenomenon

Stimulants, including Amphetamine Sulfate Tablets, used to treat ADHD are associated with peripheral vasculopathy, including Raynaud's phenomenon. Signs and symptoms are usually intermittent and mild; however, very rare sequelae include digital ulceration and/or soft tissue breakdown. Effects of peripheral vasculopathy, including Raynaud's phenomenon, were observed in post-marketing reports at different times and at therapeutic doses in all age groups throughout the course of treatment. Signs and symptoms generally improve after reduction in dose or discontinuation of drug. Careful observation for digital changes is necessary during treatment with ADHD stimulants. Further clinical evaluation (e.g., rheumatology referral) may be appropriate for certain patients.

Serotonin Syndrome

Serotonin syndrome, a potentially life-threatening reaction, may occur when amphetamines are used in combination with other drugs that affect the serotonergic neurotransmitter systems such as monoamine oxidase inhibitors (MAOIs), selective serotonin reuptake inhibitors (SSRIs), serotonin norepinephrine reuptake inhibitors (SNRIs), triptans, tricyclic antidepressants, fentanyl, lithium, tramadol, tryptophan, buspirone, and St. John's Wort (see DRUG INTERACTIONS). Amphetamines and amphetamine derivatives are known to be metabolized, to some degree, by cytochrome P450 2D6 (CYP2D6) and display minor inhibition of CYP2D6 metabolism (see CLINICAL PHARMACOLOGY). The potential for a pharmacokinetic interaction exists with the co-administration of CYP2D6 inhibitors which may increase the risk with increased exposure to Amphetamine Sulfate Tablets. In these situations, consider an alternative non-serotonergic drug or an alternative drug that does not inhibit CYP2D6 (see DRUG INTERACTIONS).

Serotonin syndrome symptoms may include mental status changes (e.g., agitation, hallucinations, delirium, and coma), autonomic instability (e.g., tachycardia, labile blood pressure, dizziness, diaphoresis, flushing, hyperthermia), neuromuscular symptoms (e.g., tremor, rigidity, myoclonus, hyperreflexia, incoordination), seizures, and/or gastrointestinal symptoms (e.g., nausea, vomiting, diarrhea).

Concomitant use of Amphetamine Sulfate Tablets with MAOI drugs is contraindicated (see CONTRAINDICATIONS).

Discontinue treatment with Amphetamine Sulfate Tablets and any concomitant serotonergic agents immediately if the above symptoms occur, and initiate supportive symptomatic treatment. If concomitant use of Amphetamine Sulfate Tablets with other serotonergic drugs or CYP2D6 inhibitors is clinically warranted, initiate Amphetamine Sulfate Tablets with lower doses, monitor patients for the emergence of serotonin syndrome during drug initiation or titration, and inform patients of the increased risk for serotonin syndrome.

Visual Disturbance

Difficulties with accommodation and blurring of vision have been reported with stimulant treatment.

PRECAUTIONS

General

Caution is to be exercised in prescribing amphetamines for patients with even mild hypertension.

The least amount feasible should be prescribed or dispensed at one time in order to minimize the possibility of overdosage.

Information for Patients

Amphetamines may impair the ability of the patient to engage in potentially hazardous activities such as operating machinery or vehicle; the patient should therefore be cautioned accordingly.

Circulation problems in fingers and toes [Peripheral vasculopathy, including Raynaud's phenomenon]

- Instruct patients beginning treatment with Amphetamine Sulfate Tablets about the risk of peripheral vasculopathy, including Raynaud's Phenomenon, and associated signs and symptoms: fingers or toes may feel numb, cool, painful, and/or may change color from pale, to blue, to red.
- Instruct patients to report to their physician any new numbness, pain, skin color change, or sensitivity to temperature in fingers or toes.
- Instruct patients to call their physician immediately with any signs of unexplained wounds appearing on fingers or toes while taking Amphetamine Sulfate Tablets.
- Further clinical evaluation (e.g., rheumatology referral) may be appropriate for certain patients.

Drug Interactions

Acidifying agents

Gastrointestinal acidifying agents (guanethidine, reserpine, glutamic acid HCl, ascorbic acid, fruit juices, etc.) lower absorption of amphetamines. Urinary acidifying agents (ammonium chloride, sodium acid phosphate, etc.) increase concentration of the ionized species of the amphetamine molecule, thereby increasing urinary excretion. Both groups of agents lower blood levels and efficacy of amphetamines.

Adrenergic blockers

Adrenergic blockers are inhibited by amphetamines.

Alkalinizing agents

Gastrointestinal alkalinizing agents (sodium bicarbonate, etc.) increase absorption of amphetamines. Urinary alkalinizing agents (acetazolamide, some thiazides) increase the concentration of the non-ionized species of the amphetamine molecule, thereby decreasing urinary excretion. Both groups of agents increase blood levels and therefore potentiate the action of amphetamines.

Antidepressants tricyclic

Amphetamines may enhance the activity of tricyclic or sympathomimetic agents; d-amphetamine with desipramine or protriptyline and possibly other tricyclics cause striking and sustained increases in the concentration of d- amphetamine in the brain; cardiovascular effects can be potentiated.

CYP2D6 Inhibitors

The concomitant use of Amphetamine Sulfate Tablets and CYP2D6 inhibitors may increase the exposure of Amphetamine Sulfate Tablets compared to the use of the drug alone and increase the risk of serotonin syndrome. Initiate with lower doses and monitor patients for signs and symptoms of serotonin syndrome particularly during Amphetamine Sulfate Tablets initiation and after a dosage increase. If serotonin syndrome occurs, discontinue Amphetamine Sulfate Tablets and the CYP2D6 inhibitor (see WARNING, OVERDOSAGE). Examples of CYP2D6 Inhibitors include paroxetine and fluoxetine (also serotonergic drugs), quinidine, ritonavir.

Serotonergic Drugs

The concomitant use of Amphetamine Sulfate Tablets and serotonergic drugs increases the risk of serotonin syndrome. Initiate with lower doses and monitor patients for signs and symptoms of serotonin syndrome, particularly during Amphetamine Sulfate Tablets initiation or dosage increase. If serotonin syndrome occurs, discontinue Amphetamine Sulfate Tablets and the concomitant serotonergic drug(s) (see WARNING and PRECAUTIONS). Examples of serotonergic drugs include selective serotonin reuptake inhibitors (SSRI), serotonin norepinephrine reuptake inhibitors (SNRI), triptans, tricyclic antidepressants, fentanyl, lithium, tramadol, tryptophan, buspirone, St. John's Wort.

MAO inhibitors

MAOI antidepressants, as well as a metabolic of furazolidone, slow amphetamine metabolism. This slowing potentiates amphetamines, increasing their affect on the release of norepinephrine and other monoamines from adrenergic nerve endings; this can cause headaches and other signs of hypertensive crisis. A variety of neurological toxic effects and malignant hyperpyrexia can occur, sometimes with fatal results.

Antihistamines

Amphetamines may counteract the sedative effect of antihistamines.

Antihypertensives

Amphetamines may antagonize the hypotensive effects of antihypertensives.

Chlorpromazine

Chlorpromazine blocks dopamine and norepinephrine reuptake, thus inhibiting the central stimulant effects of amphetamine, and can be used to treat amphetamine poisoning.

Ethosuximide

Amphetamines may delay intestinal absorption of ethosuximide.

Haloperidol

Haloperidol blocks dopamine and norepinephrine reuptake, thus inhibiting the central stimulant affects of amphetamines.

Lithium carbonate

The antiobesity and stimulatory effects of amphetamines may be inhibited by lithium carbonate.

Meperidine

Amphetamines potentiate the analgesic effect of meperidine.

Methenamine therapy

Urinary excretion of amphetamines is increased, and efficacy is reduced by acidifying agents used in methenamine therapy.

Norepinephrine

Amphetamines enhance the adrenergic effect of norepinephrine.

Phenobarbital

Amphetamines may delay intestinal absorption of Phenobarbital. Co- administration of phenobarbital may produce a synergistic anticonvulsant action.

Phenytoin

Amphetamines may delay intestinal absorption of phenytoin; co- administration of phenytoin may produce a synergistic anticonvulsant action.

Propoxyphene

In cases of propoxyphene overdosage, amphetamine CNS stimulation is potentiated and fatal convulsions can occur.

Veratrum alkaloids

Amphetamines inhibit the hypotensive effect of veratrum alkaloids.

Drug/Laboratory Test interactions

Amphetamines can cause a significant elevation in plasma corticosteroid levels. This increase is greatest in the evening. Amphetamines may interfere with urinary steroid determinations.

Carcinogenesis/Mutagenesis

Mutagenicity studies and long term studies in animals to determine the carcinogenic potential of amphetamine sulfate have not been performed.

Pregnancy

Teratogenic Effects

Dextroamphetamine sulfate has been shown to have embryotoxic and teratogenic effects when administered to A/Jax mice and C57BL mice in doses approximately 41 times the maximum human dose. Embryotoxic effects were not seen in New Zealand white rabbits given the drug in doses 7 times the human dose nor in rats given 12.5 times the maximum human dose. There are no adequate and well-controlled studies in pregnant women. Amphetamine Sulfate Tablets should be used during pregnancy only if the potential benefit justifies the potential risk to the fetus.

Nonteratogenic Effects

Infants born to mothers dependent on amphetamines have an increased risk of premature delivery and low birth weight. Also, these infants may experience symptoms of withdrawal as demonstrated by dysphoria, including agitation, and significant lassitude.

Nursing Mothers

Amphetamines are excreted in human milk. Mothers taking amphetamines should be advised to refrain from nursing.

Pediatric Use

Long-term effects of amphetamines in children have not been well established.

Amphetamines are not recommended for use as anorectic agents in children under 12 years of age, or in children under 3 years of age with Attention Deficit Disorder with Hyperactivity described under INDICATIONS AND USAGE.

Clinical experience suggests that in psychotic children, administration of amphetamines may exacerbate symptoms of behavior disturbance and thought disorder.

Amphetamines have been reported to exacerbate motor and phonic tics and Tourette's syndrome. Therefore clinical evaluation for tics and Tourette's syndrome in children and their families should precede use of stimulant medications.

Data is inadequate to determine whether chronic administration of amphetamines may be associated with growth inhibition; therefore growth should be monitored during treatment. Drug Treatment is not indicated in all cases of Attention Deficit Disorder with Hyperactivity and should be considered only in light of the complete history and evaluation of the child. The decision to prescribe amphetamines should depend on the physician's assessment of the chronicity and severity of the child's symptoms and their appropriateness for his/her age. Prescription should not depend solely on the presence of one or more of the behavioral characteristics.

When these symptoms are associated with acute stress reactions, treatment with amphetamines is usually not indicated.

ADVERSE REACTIONS

Cardiovascular

Palpitations, tachycardia, elevation of blood pressure. There have been isolated reports of cardiomyopathy associated with chronic amphetamine use.

Central Nervous System

Psychotic episodes at recommended doses (rare), overstimulation, restlessness, dizziness, insomnia, euphoria, dyskinesia, dysphoria, tremor, headache, exacerbation of motor and phonic tics and Tourette's syndrome.

Gastrointestinal

Dryness of the mouth, unpleasant taste, diarrhea, constipation, intestinal ischemia, and other gastrointestinal disturbances. Anorexia and weight loss may occur as undesirable effects when amphetamines are used for other than the anorectic effect.

Allergic

Urticaria

Endocrine

Impotence, changes in libido, and frequent or prolonged erections.

Musculoskeletal

Rhabdomyolysis

DRUG ABUSE AND DEPENDENCE

Amphetamine Sulfate Tablets are a Schedule II controlled substance. Amphetamines have been extensively abused. Tolerance, extreme psychological dependence, and severe social disability have occurred. There are reports of patients who have increased the dosage to many times the recommended. Abrupt cessation following prolonged high dosage administration results in extreme fatigue and mental depression; changes are also noted on the sleep EEG. Manifestations of chronic intoxication with amphetamines include severe dermatosis, marked insomnia, irritability, hyperactivity and personality changes. The most severe manifestation of chronic intoxication is psychosis, often clinically indistinguishable from schizophrenia. This is rare with oral amphetamines.

OVERDOSAGE

Individual patient response to amphetamines varies widely. While toxic symptoms occasionally occur as an idiosyncrasy at doses as low as 2 mg, they are rare with doses of less than 15 mg; 30 mg can produce severe reactions, yet doses of 400 to 500 mg are not necessarily fatal.

In rats, the oral LD50 of dextroamphetamine sulfate is 96.8 mg/Kg.

Symptoms

Manifestations of acute overdosage with amphetamines include restlessness, tremor, hyperreflexia, rhabdomyolysis, rapid respiration, hyperpyrexia, confusion, assaultiveness, hallucinations, panic states. Fatigue and depression usually follow the central stimulation. Cardiovascular effects include arrhythmias, hypertension, or hypotension and circulatory collapse. Gastrointestinal symptoms include nausea, vomiting, diarrhea, and abdominal cramps. Fatal poisoning is usually preceded by convulsions and coma.

Treatment

Management of acute amphetamine intoxication is largely symptomatic and includes gastric lavage and sedation with a barbiturate. Experience with hemodialysis or peritoneal dialysis is inadequate to permit recommendation in this regard. Acidification of the urine increases amphetamine excretion. If acute, severe hypertension complicates amphetamine overdosage, administration of intravenous phentolamine has been suggested. However, a gradual drop in blood pressure will usually result when sufficient sedation has been achieved. Chlorpromazine antagonizes the central stimulant effects of amphetamines and can be used to treat amphetamine intoxication.

DOSAGE AND ADMINISTRATION

Regardless of indication, amphetamine should be administered at the lowest effective dosage and dosage should be individually adjusted. Late evening doses should be avoided because of resulting insomnia.

Narcolepsy

Usual dose is 5 to 60 milligrams per day in divided doses depending on the individual patient response.

Narcolepsy seldom occurs in children under 12 years of age; however, when it does, Amphetamine Sulfate Tablets may be used. The suggested initial dose for patients aged 6 to 12 is 5 mg daily; daily dose may be raised in increments of 5 mg at weekly intervals until optimal response obtained. In patients 12 years of age and older, start with 10 mg daily; daily dosage may be raised in increments of 10 mg at weekly intervals until optimal response is obtained. If bothersome adverse reactions appear (e.g., insomnia or anorexia) dosage should be reduced. Give the first dose on awakening; additional doses (5 or 10 mg) at intervals of 4 to 6 hours.

Attention Deficit Disorder with Hyperactivity

Not recommended for children under 3 years of age.

In children from 3 to 5 years of age, start with 2.5 mg daily; daily dosage may be raised in increments of 2.5 mg at weekly intervals until optimal response is obtained.

In children 6 years of age or older, start with 5 mg once or twice daily; daily dosage may be raised in increments of 5 mg at weekly intervals until optimal response is obtained. Only in rare cases will it be necessary to exceed a total of 40 milligrams per day.

With tablets give first dose on awakening; additional doses (1 to 2) at intervals of 4 to 6 hours.

Where possible, drug administration should be interrupted occasionally to determine if there is a recurrence of behavioral symptoms sufficient to require continued therapy.

Exogenous Obesity

Usual dosage is up to 30 mg daily, taken in divided doses of 5 to 10 mg, 30 to 60 minutes before meals. Not recommended for this use in children under 12 years of age.

HOW SUPPLIED

Amphetamine Sulfate Tablets, USP, are supplied as follows:

10 mg: Blue, round tablet, debossed "EVK" on one side, and "10" with double scores on the other side in:

Bottles of 100 tablets, NDC 63629-2498-1

Store at 20° to 25°C (68° to 77°F). [See USP Controlled Room Temperature.]
Dispense in a well-closed container, as defined in the USP.

Repackaged/Relabeled by:
Bryant Ranch Prepack, Inc.
Burbank, CA 91504

Manufactured for:
Wilshire Pharmaceuticals, Inc.
Atlanta, GA 30328
AMAG-PI-02

Rev. 02/22

MEDICATION GUIDE Amphetamine Sulfate Tablets, USP

Read this Medication Guide before you or your child starts taking Amphetamine Sulfate Tablets and each time you get a refill. There may be new information. This information does not take the place of talking to your doctor about you or your child's treatment.

What is the most important information I should know about Amphetamine Sulfate Tablets?

Amphetamine Sulfate Tablets are a stimulant medicine. Some people have had the following problems when taking stimulant medicines such as Amphetamine Sulfate Tablets:

1. Heart-related problems:

- sudden death in people who have heart problems or heart defects
- stroke and heart attack in adults
- increased blood pressure and heart rate

Tell your doctor if you or your child has any heart problems, heart defects, high blood pressure, or a family history of these problems.

Your doctor should check you or your child carefully for heart problems before starting Amphetamine Sulfate Tablets.

Your doctor should check you or your child's blood pressure and heart rate regularly during treatment with Amphetamine Sulfate Tablets.

Call your doctor right away if you or your child have any signs of heart problems such as chest pain, shortness of breath, or fainting while taking Amphetamine Sulfate Tablets.

2. Mental (Psychiatric) problems including:

In children, teenagers, and adults:

- new or worse behavior and thought problems
- new or worse bipolar illness
- new or worse aggressive behavior or hostility

In Children and Teenagers who have psychiatric problems, new psychotic symptoms such as:

- hearing voices
- seeing things that are not real
- believing things that are not true
- being suspicious
- new manic symptoms

Tell your doctor about any mental problems you or your child have, or about a family history of suicide, bipolar illness, or depression.

Call your doctor right away if you or your child have any new or worsening mental symptoms or problems while taking Amphetamine Sulfate Tablets, especially:

- seeing or hearing things that are not real
- believing things that are not real
- being suspicious

3. Circulation problems in fingers and toes [Peripheral vasculopathy, including Raynaud's phenomenon].

- Fingers or toes may feel numb, cool, painful
- Fingers or toes may change color from pale, to blue, to red

Tell your doctor if you have or your child has numbness, pain, skin color change, or sensitivity to temperature in your fingers or toes.

Call your doctor right away if you have or your child has any signs of unexplained wounds appearing on fingers or toes while taking Amphetamine Sulfate Tablets.

What are Amphetamine Sulfate Tablets?

- Amphetamine Sulfate Tablets are a central nervous system stimulant prescription medicine used for the treatment of:
  - a sleep disorder called narcolepsy.
  - Attention-Deficit Hyperactivity Disorder (ADHD).
    Amphetamine Sulfate Tablets may help increase attention and decrease impulsiveness and hyperactivity in patients with ADHD. Amphetamine Sulfate Tablets should be used as part of a total treatment program for ADHD that may include counseling or other therapies.
  - exogenous obesity. Amphetamine Sulfate Tablets may be used as part of a short-term, weight reduction program for obesity.
- Amphetamine Sulfate Tablets are not for use as an anorectic agent for exogenous obesity in children less than 12 years of age.
- Amphetamine Sulfate Tablets are not for use for ADHD in children less than 3 years old.
- The effects of long term use of Amphetamine Sulfate Tablets in children are not known.

Amphetamine Sulfate Tablets are a federally controlled substance (CII) because they contain amphetamine that can be a target for people who abuse prescription medicines or street drugs. Keep Amphetamine Sulfate Tablets in a safe place to protect them from theft. Never give your Amphetamine Sulfate Tablets to anyone else, because they may cause death or harm them. Selling or giving away Amphetamine Sulfate Tablets is against the law.

Tell your doctor if you or your child has (or has a family history of) ever abused or been dependent on alcohol, prescription medicines or street drugs.

Who should not take Amphetamine Sulfate Tablets?

Do not take Amphetamine Sulfate Tablets if you or your child:

- have heart problems or hardening of the arteries
- have moderate to severe high blood pressure
- have hyperthyroidism
- are very anxious, tense, or agitated
- have a history of drug abuse
- are taking or have taken within the past 14 days an anti-depression medicine called a monoamine oxidase inhibitor or MAOI
- are sensitive to, allergic to, or had a reaction to other stimulant medicines

What should I tell my doctor before taking Amphetamine Sulfate Tablets?

Before you or your child takes Amphetamine Sulfate Tablets, tell your doctor if you or your child has or if there is a family history of:

- heart problems, heart defects, high blood pressure
- mental problems including psychosis, mania, bipolar illness, or depression
- tics or Tourette's syndrome
- thyroid problems
- seizures or have had an abnormal brain wave test (EEG)
- circulation problems in fingers and toes

Tell your doctor if:

- you or your child are pregnant or planning to become pregnant. It is not known if Amphetamine Sulfate Tablets will harm your unborn baby.
- you or your child are breastfeeding or plan to breastfeed. Amphetamine Sulfate Tablets can pass into your milk and may harm your baby. Talk to your doctor about the best way to feed your baby if you take Amphetamine Sulfate Tablets. Do not breastfeed while taking Amphetamine Sulfate Tablets.

Tell your doctor about all the medicines that you or your child takes, including prescription and nonprescription medicines, vitamins, and herbal supplements.

Amphetamine Sulfate Tablets and some medicines may interact with each other and cause serious side effects. Sometimes the doses of other medicines will need to be adjusted while taking Amphetamine Sulfate Tablets.

Your doctor will decide whether Amphetamine Sulfate Tablets can be taken with other medicines.

Especially tell your doctor if you or your child takes:

- stomach acid medicines
- anti-depression medicines including MAOIs
- anti-psychotic medicines
- lithium
- cold or allergy medicines that contain decongestants
- blood pressure medicines
- narcotic pain medicines
- seizure medicines
- blood thinner medicines

Know the medicines that you or your child takes.

Keep a list of your medicines with you to show your doctor and pharmacist when you get a new medicine.

Do not start any new medicine while taking Amphetamine Sulfate Tablets without talking to your doctor first.

How should I take Amphetamine Sulfate Tablets?

- Take Amphetamine Sulfate Tablets exactly as your doctor tells you to take it.
- Your doctor may change the dose until it is right for you or your child.
- The first dose of the day is usually taken when you first wake in the morning.
- Amphetamine Sulfate Tablets may cause problems sleeping if taken late at night.
- Amphetamine Sulfate Tablets can be taken with or without food.
- From time to time, your doctor may stop Amphetamine Sulfate Tablets treatment for a while to check ADHD symptoms.
- Your doctor may do regular checks of the blood, heart, and blood pressure while taking Amphetamine Sulfate Tablets.
- Children should have their height and weight checked often while taking Amphetamine Sulfate Tablets. Amphetamine Sulfate Tablets treatment may be stopped if a problem is found during these check-ups.
- If you or your child takes too many Amphetamine Sulfate Tablets, call your doctor right away, or go to the nearest hospital emergency room.

What should I avoid while taking Amphetamine Sulfate Tablets?

Do not drive, operate machinery, or do other dangerous activities until you know how Amphetamine Sulfate Tablets affect you.

What are possible side effects of Amphetamine Sulfate Tablets?

Amphetamine Sulfate Tablets may cause serious side effects, including:

See "What is the most important information I should know about Amphetamine Sulfate Tablets?" for information on reported heart and mental problems.

Other serious side effects include:

- slowing of growth (height and weight) in children
- seizures, mainly in people with a history of seizures
- eyesight changes or blurred vision
- Serotonin syndrome. A potentially life-threatening problem called serotonin syndrome can happen when medicines such as Amphetamine Sulfate Tablets are taken with certain other medicines. Symptoms of serotonin syndrome may include:
  - agitation, hallucinations, coma or other changes in mental status
  - problems controlling your movements or muscle twitching
  - fast heartbeat
  - high or low blood pressure
  - sweating or fever
  - nausea or vomiting
  - diarrhea
  - muscle stiffness or tightness

The most common side effects of Amphetamine Sulfate Tablets include:

- headache
- stomach ache
- trouble sleeping
- decreased appetite
- unpleasant taste
- nervousness
- dizziness
- sexual problems (impotence in males)
- vomiting
- itching
- diarrhea or constipation
- dry mouth
- weight loss
- mood swings

Talk to your doctor if you or your child have side effects that are bothersome or do not go away.

These are not all the possible side effects of Amphetamine Sulfate Tablets. For more information ask your doctor or pharmacist.

Call your doctor for medical advice about side effects. You may report side effects to Wilshire Pharmaceuticals, Inc., Medical Information at 1-877-495-6856 or FDA at 1-800-FDA-1088.

How should I store Amphetamine Sulfate Tablets?

- Store Amphetamine Sulfate Tablets at room temperature between 68˚F to 77˚F (20˚C to 25˚C).
- Keep Amphetamine Sulfate Tablets and all medicines out of the reach of children.

General information about the safe and effective use of Amphetamine Sulfate Tablets.

Medicines are sometimes prescribed for purposes other than those listed in a Medication Guide. Do not use Amphetamine Sulfate Tablets for a condition for which they were not prescribed. Do not give Amphetamine Sulfate Tablets to other people, even if they have the same condition. It may harm them and it is against the law.

This Medication Guide summarizes the most important information about Amphetamine Sulfate Tablets. If you would like more information, talk with your doctor. You can ask your doctor or pharmacist for information about Amphetamine Sulfate Tablets that was written for healthcare professionals.

For more information about Amphetamine Sulfate Tablets, please contact Wilshire Pharmaceuticals, Inc. at 1-877-495-6856.

What are the ingredients in Amphetamine Sulfate Tablets?

Active Ingredient: amphetamine sulfate

Inactive Ingredients: crospovidone, silicified microcrystalline cellulose, and stearic acid. The 10 mg tablets also contain FD&C Blue #1.

This Medication Guide has been approved by the U.S. Food and Drug Administration.

Manufactured for:
Wilshire Pharmaceuticals, Inc.
Atlanta, GA 30328
AMAG-MG-01

Rev. 11/19

PACKAGE LABEL

Amphetamine Sulfate (CII) 10 mg Tab, #100